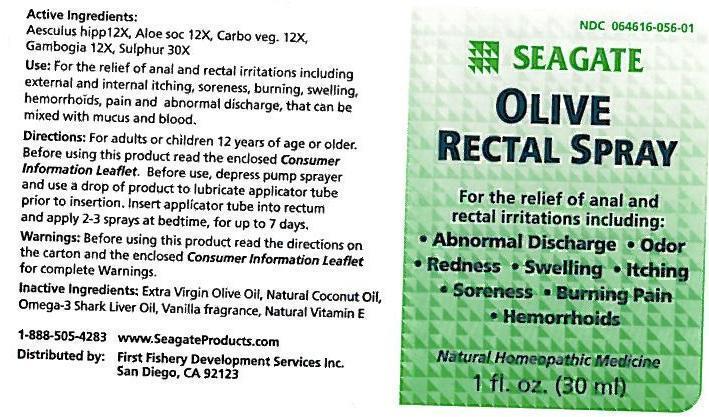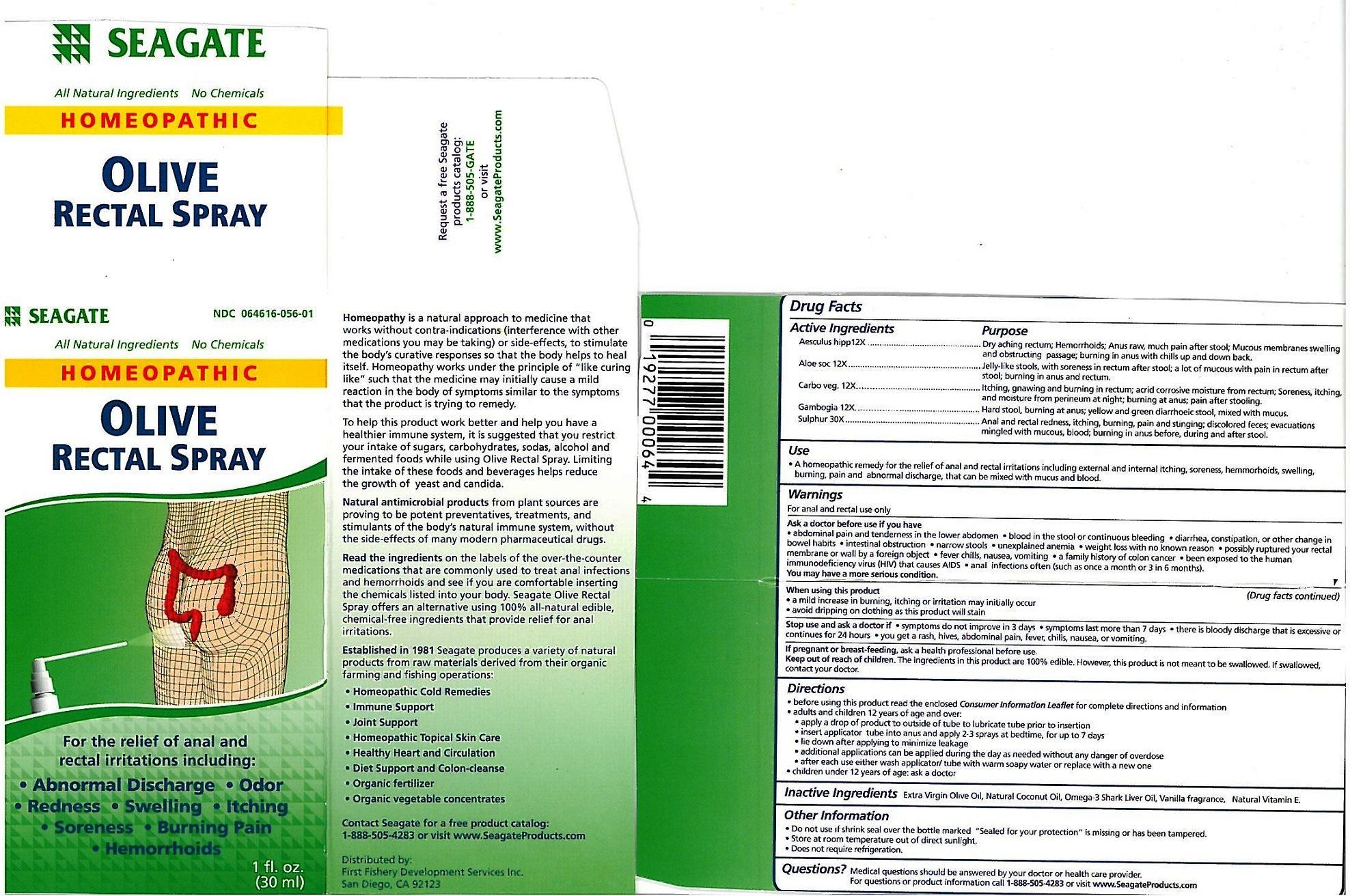 DRUG LABEL: Olive Rectal Formula
NDC: 64616-056 | Form: SPRAY
Manufacturer: Vitality Works, Inc.
Category: homeopathic | Type: HUMAN PRESCRIPTION DRUG LABEL
Date: 20171206

ACTIVE INGREDIENTS: HORSE CHESTNUT 12 [hp_X]/1 mL; ALOE 12 [hp_X]/1 mL; ACTIVATED CHARCOAL 12 [hp_X]/1 mL; GAMBOGE 12 [hp_X]/1 mL; SULFUR 30 [hp_X]/1 mL
INACTIVE INGREDIENTS: OLIVE OIL; COCONUT OIL; ALPHA-TOCOPHEROL; SHARK LIVER OIL; VANILLA

Olive Rectal Spray

Olive Rectal Spray

Aesculius hipp 12X

Aloe soc 12X

Carbo veg 12X

Gambogia 12X

Sulphur 30X

Olive Rectal Spray

Extra Virgin Olive Oil, Natural Coconut Oil, Omega-3 Shark Live Oil, Vanilla fragrance, Natural Vitamin E

Olive Rectal Spray

Ask a doctor before use if you have:

- abdominal pain and tenderness in the lower abdomen

- Blood in the stool or continuous bleeding

- diarrhea, constipation, or other change in bowel habits

- intestinal obstruction

-narrow stools

- weight loss with no known reason

-possibly ruptured your rectal membrane or wall by a foreign object

-fever chillis, nausea, vomiting

- a family history of colon cancer

- been exposed to the human immunodefiency virus (HIV) that causes AIDS

-anal infections often (such as once a month or 3 in 6 months)

Olive Rectal Spray

Keep out of reach of children. The ingredients in this product are 100% edible. However, this product is not meant to be swallowed, If swallowed, contact your doctor

Olive Rectal Spray

A homeopathic remedy for the relief of anal and rectal irritations including external and internal itching, soreness, hemmorhoid, swelling, buring pain and abnormal dischare, that can be mixed with mucus and blood.

Olive Rectal Spray

Adults and children 12 years of age and over.

-apply a drop of product to outside of tube to lubricate tube prior to insertion.

-insert applicater tube into anus and apply 2-3 sprays at bedtime for up to 7 days

-lie down after applying to minimize leakage

-additiona applications can be applied during the day as needed without any danger of overdose

-After each use either wash applicator/tube with warm soapy water of replace with a new one

Children under 12 years of age, ask a doctor.

Olive Rectal Spray

Aesculus hipp - Dry aching rectum, Hemmorrhoids; anus raw, much pain after stool; Mucous membranes swelling and obstructing passage; buring in anus with chills up and down back.

Aloe soc - Jelly-like stoos, with soreness in rectum after stool; mixed with mucus

Carbo veg - itching, gnawing and burning in rectum; acrid corrosive moisture from rectum; Soreness, itching, and moister from perineum at night; buring at anus; pain after stooling

Gambogia - Hard stool, burning at anus, yellow and green diarrhoeic stool, mixed with mucus.

Sulpher - Anal and rectoal redness, itching, burning, pain, and stinging; discolored feces, evacuations mingled with mucous, blood; buring in anus during and after stool